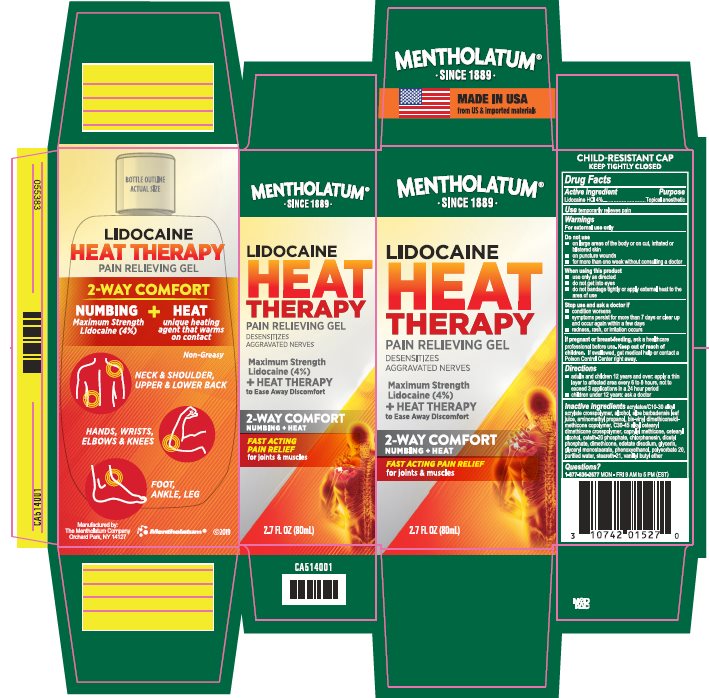 DRUG LABEL: Mentholatum Lidocaine Heat
NDC: 10742-8386 | Form: CREAM
Manufacturer: The Mentholatum Company
Category: otc | Type: HUMAN OTC DRUG LABEL
Date: 20241217

ACTIVE INGREDIENTS: LIDOCAINE HYDROCHLORIDE 40 mg/1 mL
INACTIVE INGREDIENTS: CARBOMER INTERPOLYMER TYPE A (ALLYL SUCROSE CROSSLINKED); ALCOHOL; ALOE VERA LEAF; AMINOMETHYLPROPANOL; DIMETHICONE/VINYL DIMETHICONE CROSSPOLYMER (SOFT PARTICLE); CAPRYLYL TRISILOXANE; CETOSTEARYL ALCOHOL; CETETH-20 PHOSPHATE; CHLORPHENESIN; DIHEXADECYL PHOSPHATE; DIMETHICONE; EDETATE DISODIUM; GLYCERIN; GLYCERYL MONOSTEARATE; PHENOXYETHANOL; POLYSORBATE 20; WATER; STEARETH-21; VANILLYL BUTYL ETHER

Drug Facts - Mentholatum Lidocaine Heat

Active ingredients

Lidocaine HCl 4%

Purpose

Lidocaine HCl - Topical anesthetic

Uses

temporarily relieves pain

Warnings

For external use only

Do not use

- on large areas of the body or on cut, irritated or blistered skin
- on puncture wounds
- for more than one week without consulting a doctor

When using this product

- use only as directed
- do not get into eyes
- do not bandage tightly or apply external heat to the area of use

Stop use and ask a doctor if

- condition worsens
- symptoms persist for more than 7 days or clear up and occur again within a few days
- redness, rash, or irritation occurs

If pregnant or breast-feeding,

ask a health professional before use.

Keep out of reach of children.

If swallowed, get medical help or contact a Poison Control Center right away.

Directions

- adults and children 12 years and over: apply a thin layer to affected area every 6 to 8 hours, not to exceed 3 applications in a 24 hour period
- children under 12 years: ask a doctor

Inactive ingredients

acrylates/C10-30 alkyl acrylate crosspolymer, alcohol, aloe barbadensis leaf juice, aminomethyl propanol, bis-vinyl dimethicone/dimethicone copolymer, C30-45 alkyl cetearyl dimethicone crosspolymer, caprylyl methicone, cetearyl alcohol, ceteth-20 phosphate, chlorphenesin, dicetyl phosphate, dimethicone, edetate disodium, glycerin, glyceryl monostearate, phenoxyethanol, polysorbate 20, purified water, steareth-21, vanillyl butyl ether